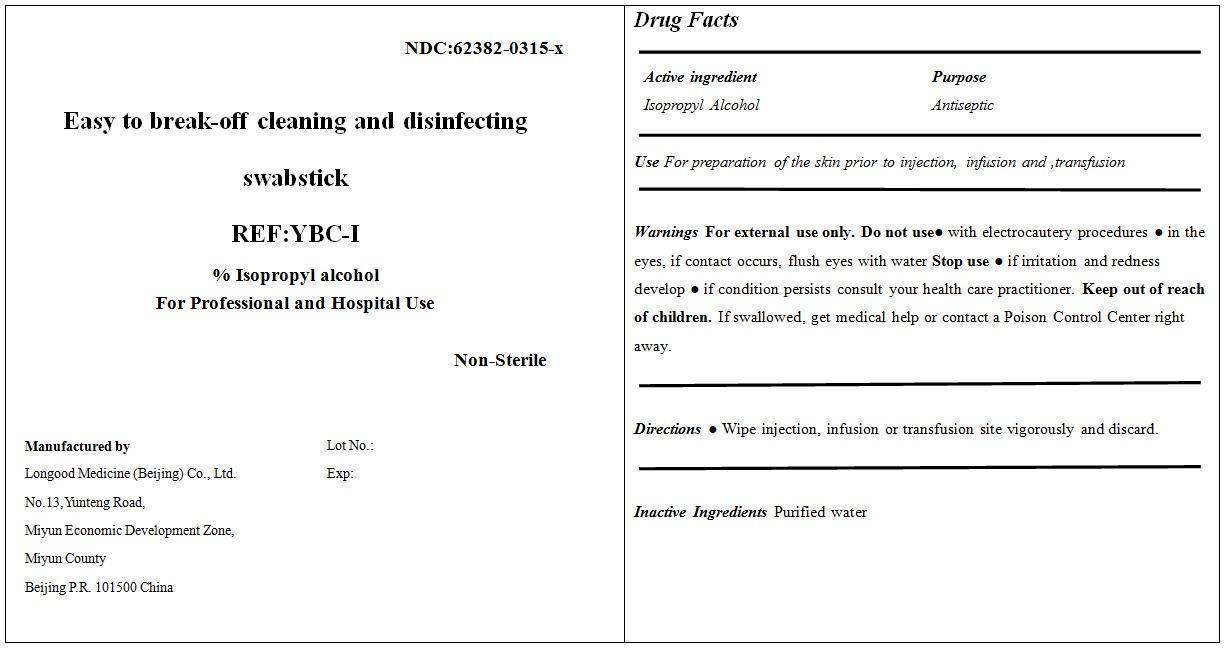 DRUG LABEL: Easy to break-off cleaning and disinfecting swabstick YBC-I
NDC: 62382-0315 | Form: SWAB
Manufacturer: Longood Medicine (Beijing) Co., Ltd.
Category: otc | Type: HUMAN OTC DRUG LABEL
Date: 20200106

ACTIVE INGREDIENTS: ISOPROPYL ALCOHOL 0.7 mL/1 mL
INACTIVE INGREDIENTS: WATER 0.3 mL/1 mL

Drug Fact

PACKAGE LABEL

Active ingredient

Isopropyl Alcohol 70%

Purpose

Antiseptic

Use

For preparation of the skin prior to injection, infusion and ,transfusion

Dosage

SWAB

Warnings

For external use only.

Do not use

● with electrocautery procedures

● in the eyes, if contact occurs, flush eyes with water

Stop Use

● if irritation and redness develop

● if condition persists consult your health care practitioner

Keep out of reach of children

. If swallowed, get medical help or contact a Poison Control Center right away.

Directions

Wipe injection, infusion or transfusion site vigorously and discard.

Inactive Ingredients

Purified water